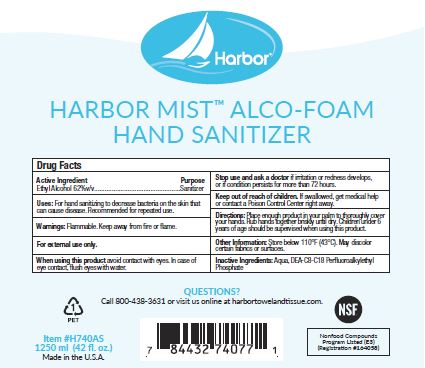 DRUG LABEL: Harbor Mist Alco-Foam Hand Sanitizer
NDC: 81792-003 | Form: LIQUID
Manufacturer: Von Drehle Corporation
Category: otc | Type: HUMAN OTC DRUG LABEL
Date: 20241125

ACTIVE INGREDIENTS: ALCOHOL 62 mL/100 mL
INACTIVE INGREDIENTS: DIETHANOLAMINE BIS(C8-C18 PERFLUOROALKYLETHYL)PHOSPHATE; WATER

81792-003

Active Ingredient

Ethyl Alcohol 62%v/v

Purpose

Sanitizer

Uses:

For hand sanitizing to decrease bacteria on the skin that can cause disease.

Recommended for repeated uses.

Warnings:

Flammable. Keep away from fire or flame.

For external use only.

When using this productavoid contact with eyes.

In case of eye contact, flush eyes with water.

Stop use and ask a doctorif irritation or redness develops, or condition persists for more than 72 hours.

Keep out of reach of children.

If swallowed, get medical help or contact a Poison Control Center right away.

Directions:

Place enough product in your palm to thoroughly cover your hands.

Rub hands together briskly until dry.

Children under 6 yearsof age should be supervised when using this product.

Other Information:

Store below 110 F (43 C).

May discolor certain fabrics or surfaces.

Inactive Ingredients:

Aqua, DEA-C8-C18 Perfluoroalkylethyl Phosphate

PACKAGE LABEL

Harbor

HARBOR MIST ALCO-FOAM

HAND SANITIZER

QUESTIONS?

Call 800-438-3631 or visit us online at harbortowelandtissue.com.

1

PET

NSF

Nonfood Compounds

Program Listed (E3)

(Registration #164058)

Item #H740AS

1250 ml (42 fl. oz.)

Made in the U.S.A.